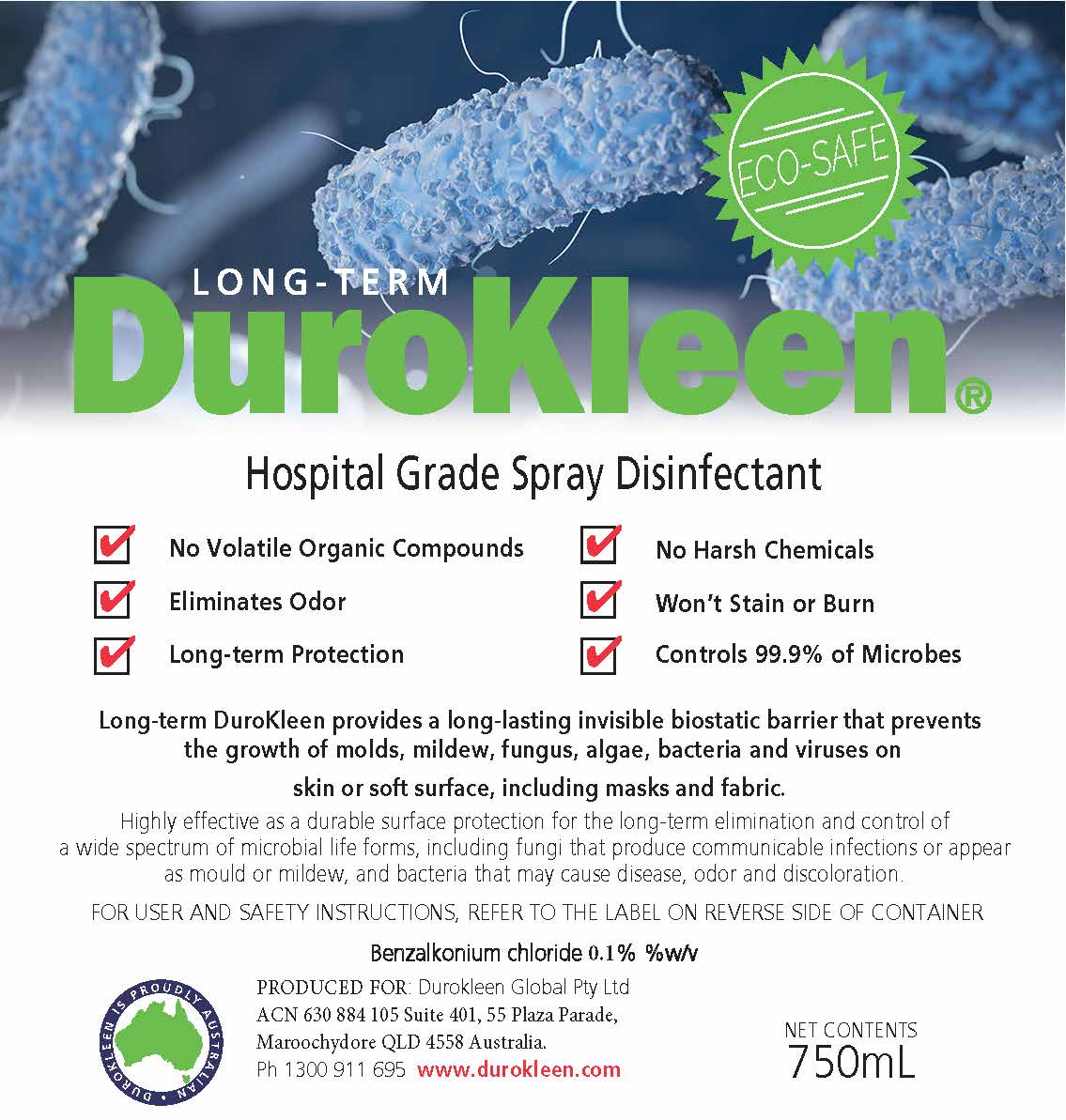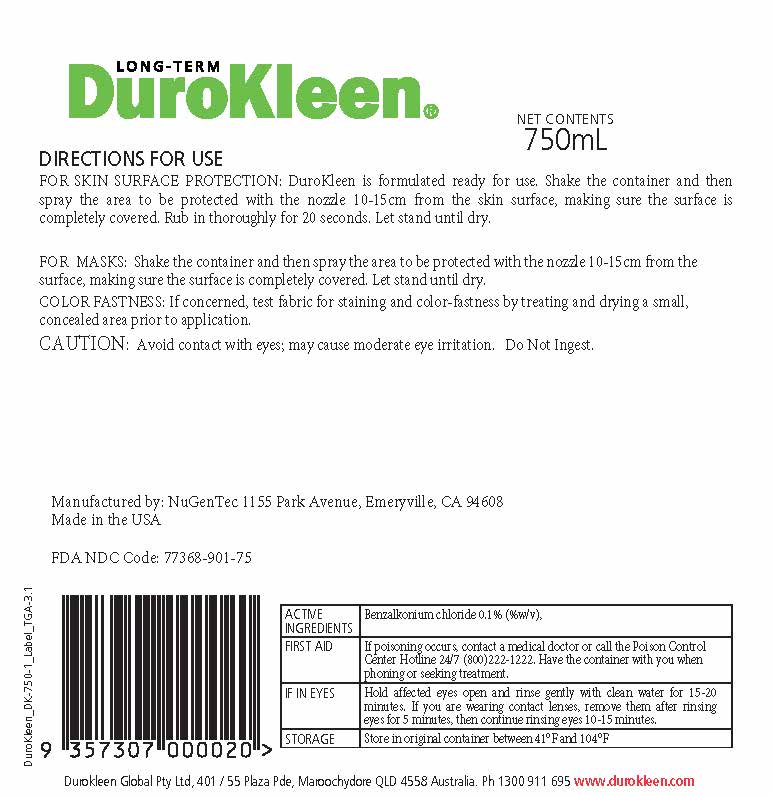 DRUG LABEL: DuroKleen Sanitizer
NDC: 77368-902 | Form: LIQUID
Manufacturer: NuGenTec
Category: otc | Type: HUMAN OTC DRUG LABEL
Date: 20210125

ACTIVE INGREDIENTS: BENZALKONIUM CHLORIDE 0.1 mg/100 mL
INACTIVE INGREDIENTS: DIMETHYLTETRADECYL(3-(TRIMETHOXYSILYL)PROPYL)AMMONIUM CHLORIDE 0.2 mL/100 mL; WATER

DuroKleen Sanitizing Spray

Active Ingredient(s)

Benzalkonium Chloride 0.10%

Purpose

Antiseptic, Hand Sanitizer, Antibacterial

Use

Hand Sanitizer to help reduce bacteria that potentially can cause disease. For use when soap and water are not available.

Warnings

For external use only. Flammable. Keep away from heat or flame

Do not use

- in children less than 2 months of age
- on open skin wounds

When using this product keep out of eyes, ears, and mouth. In case of contact with eyes, rinse eyes thoroughly with water.
Stop use and ask a doctor if irritation or rash occurs. These may be signs of a serious condition.
Keep out of reach of children. If swallowed, get medical help or contact a Poison Control Center right away.

Stop use and ask a doctor if irritation or rash occurs. These may be signs of a serious condition.

Keep out of reach of children. If swallowed, get medical help or contact a Poison Control Center right away.

Directions

- Spray product on hands to cover and wet all surfaces. Rub thoroughly. Allow to dry without wiping
- Supervise children under 6 years of age when using this product to avoid swallowing.

Other information

- Store between 15-30C (59-86F)
- Avoid freezing and excessive heat above 40C (104F)

Inactive ingredients

Ztrex 72 MUP, purified water USP

Package Label - Principal Display Panel

750mL is one bottle NDC: 77368-901-75